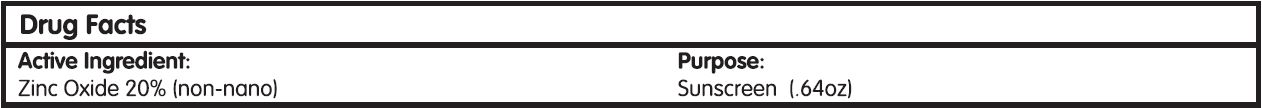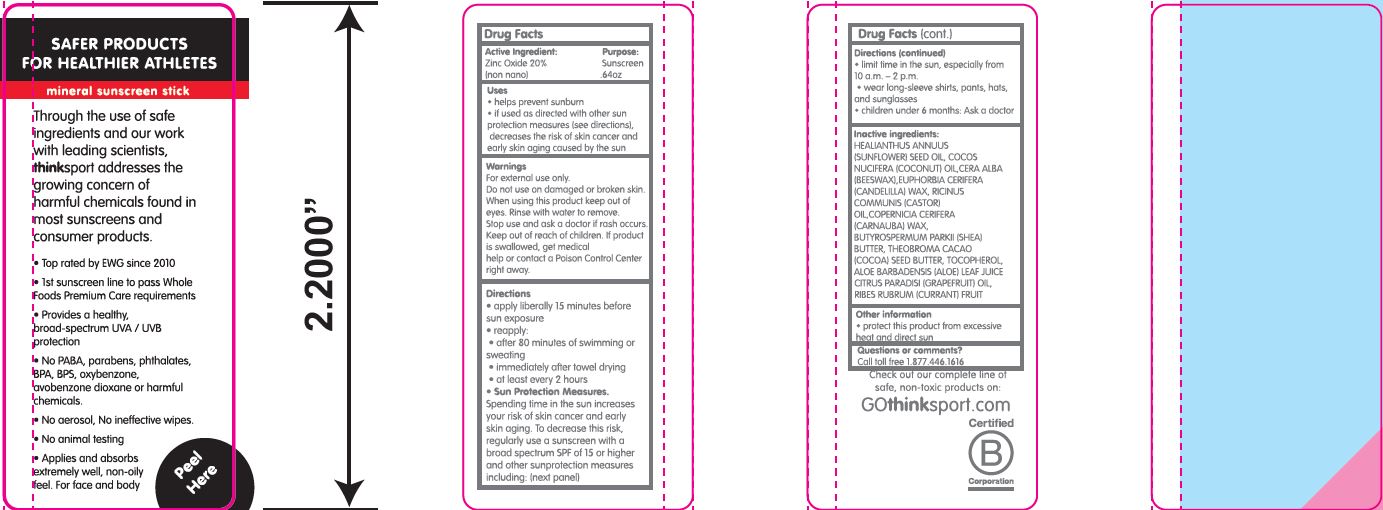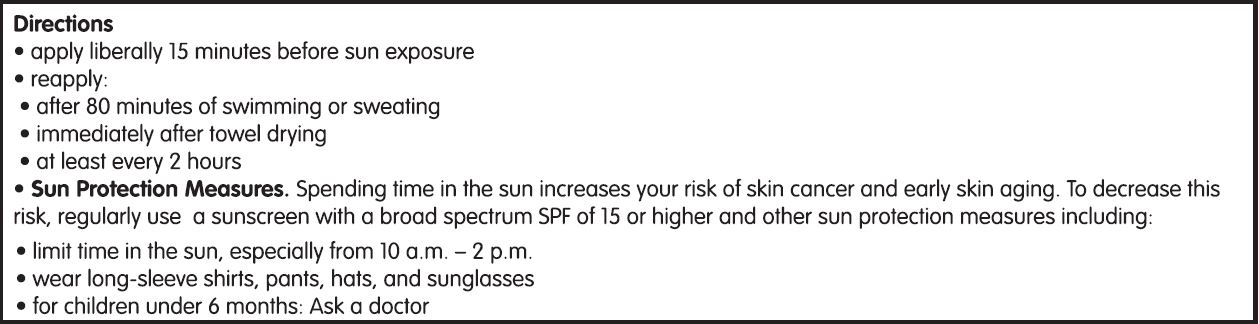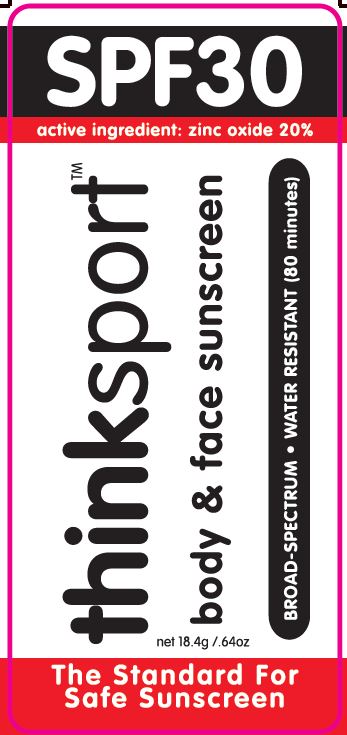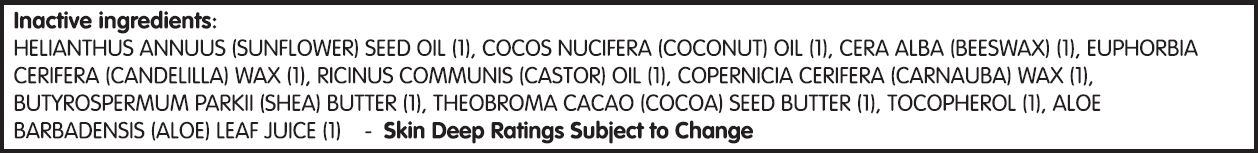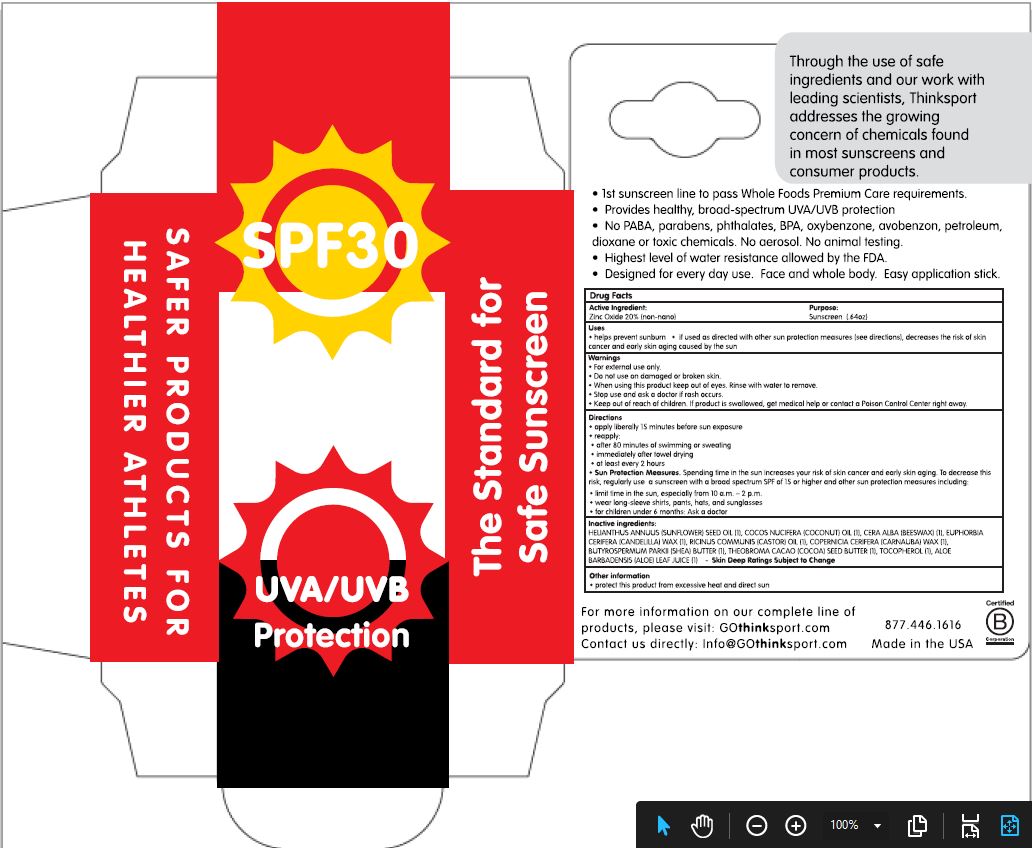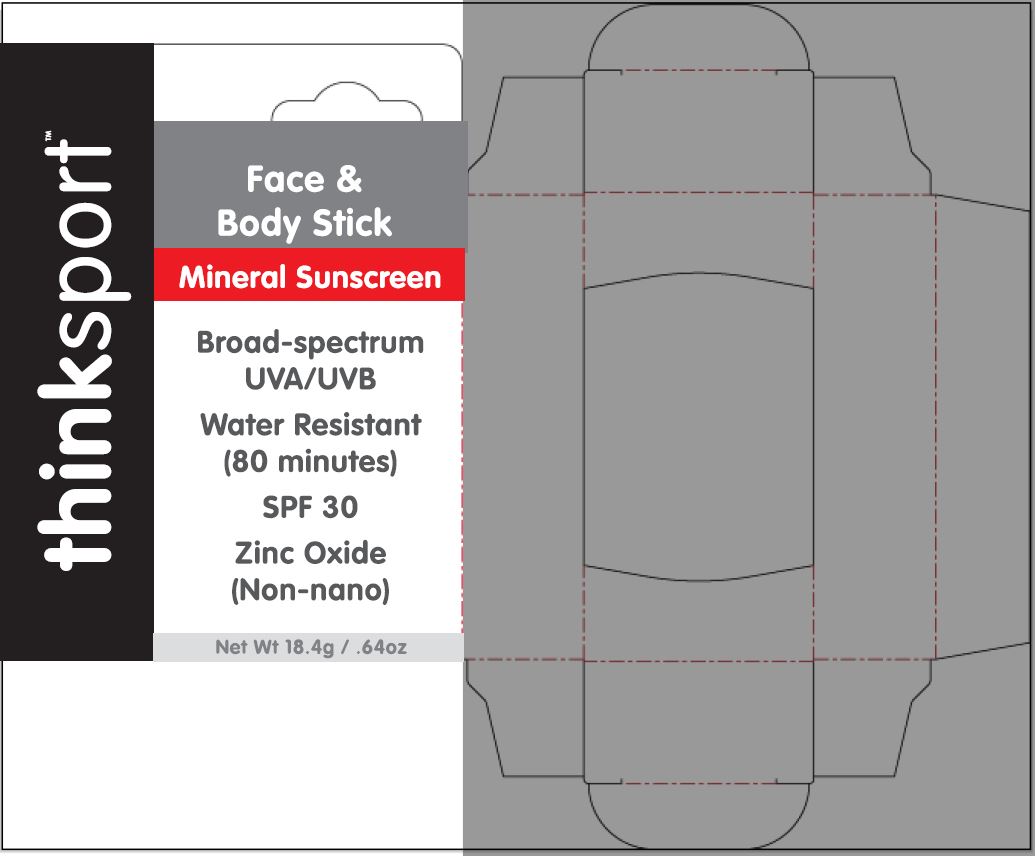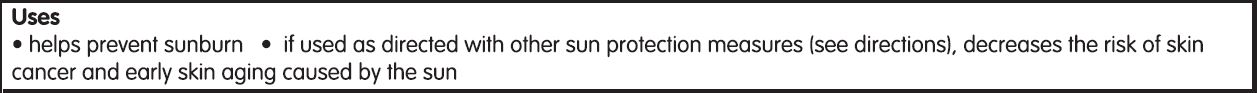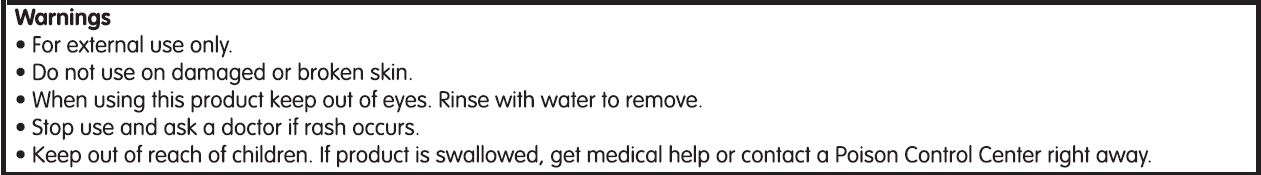 DRUG LABEL: Think Sport SPF 30
NDC: 62932-265 | Form: STICK
Manufacturer: Private Label Select Ltd CO
Category: otc | Type: HUMAN OTC DRUG LABEL
Date: 20220104

ACTIVE INGREDIENTS: ZINC OXIDE 20 g/100 g
INACTIVE INGREDIENTS: COCONUT OIL; CASTOR OIL; SHEA BUTTER; COCOA BUTTER; ALOE VERA LEAF; .ALPHA.-TOCOPHEROL, D-; .BETA.-TOCOPHEROL; .GAMMA.-TOCOPHEROL; CARNAUBA WAX; .DELTA.-TOCOPHEROL; SUNFLOWER OIL; WHITE WAX; CANDELILLA WAX

Think Operations, Think Sport SPF 30